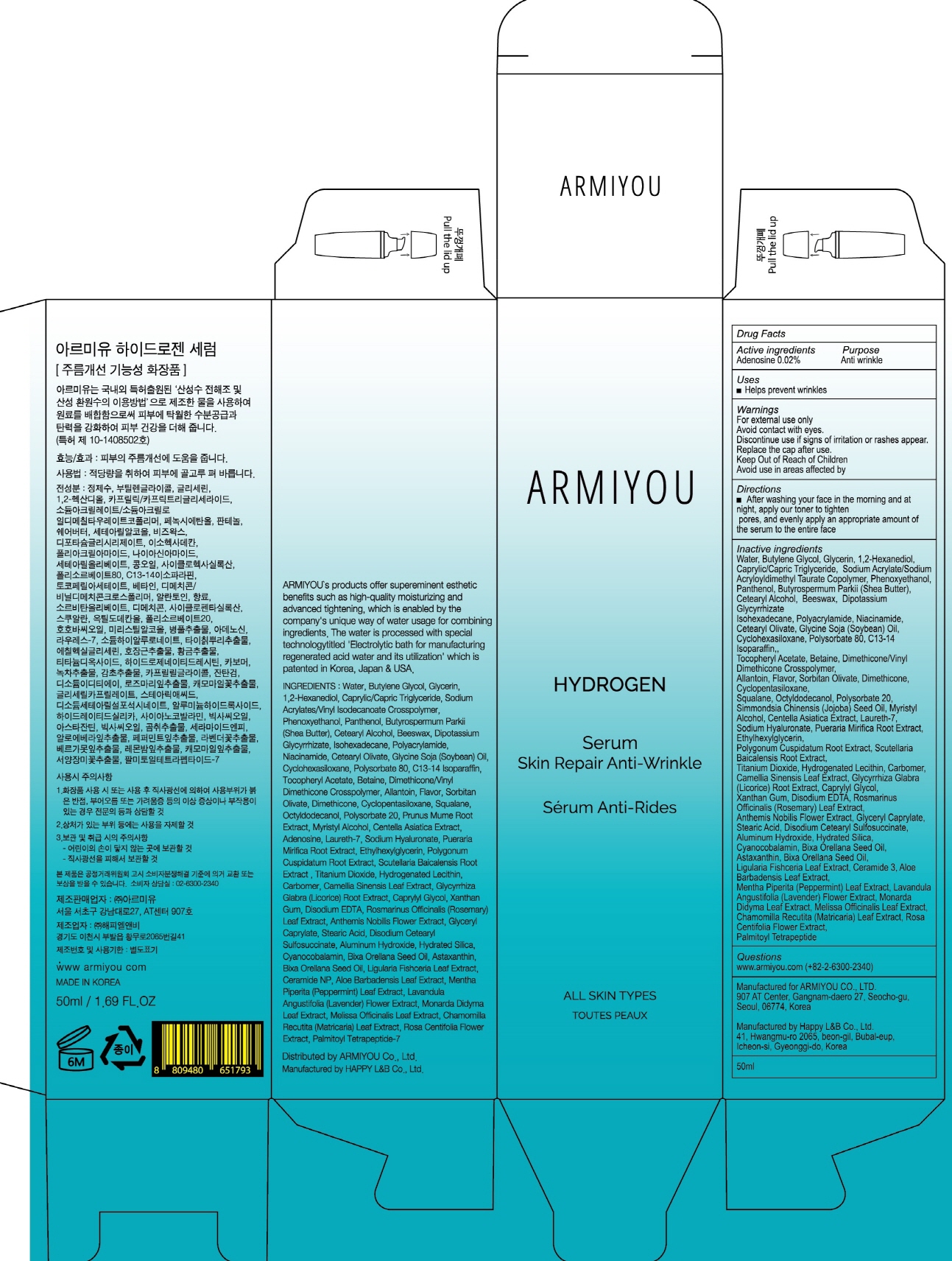 DRUG LABEL: ARMIYOU HYDROGEN SERUM
NDC: 71878-020 | Form: CREAM
Manufacturer: Armiyou
Category: otc | Type: HUMAN OTC DRUG LABEL
Date: 20171122

ACTIVE INGREDIENTS: Adenosine 0.01 g/50 mL
INACTIVE INGREDIENTS: Water; Butylene Glycol

ACTIVE INGREDIENT

Active ingredients: Adenosine 0.02%

INACTIVE INGREDIENT

Inactive ingredients: Water, Butylene Glycol, Glycerin, 1,2-Hexanediol, Caprylic/Capric Triglyceride, Sodium Acrylate/Sodium Acryloyldimethyl Taurate Copolymer, Phenoxyethanol, Panthenol, Butyrospermum Parkii (Shea Butter), Cetearyl Alcohol, Beeswax, Dipotassium Glycyrrhizate Isohexadecane, Polyacrylamide, Niacinamide, Cetearyl Olivate, Glycine Soja (Soybean) Oil, Cyclohexasiloxane, Polysorbate 80, C13-14 Isoparaffin,, Tocopheryl Acetate, Betaine, Dimethicone/Vinyl Dimethicone Crosspolymer, Allantoin, Flavor, Sorbitan Olivate, Dimethicone, Cyclopentasiloxane, Squalane, Octyldodecanol, Polysorbate 20, Simmondsia Chinensis (Jojoba) Seed Oil, Myristyl Alcohol, Centella Asiatica Extract, Laureth-7, Sodium Hyaluronate, Pueraria Mirifica Root Extract, Ethylhexylglycerin, Polygonum Cuspidatum Root Extract, Scutellaria Baicalensis Root Extract, Titanium Dioxide, Hydrogenated Lecithin, Carbomer, Camellia Sinensis Leaf Extract, Glycyrrhiza Glabra (Licorice) Root Extract, Caprylyl Glycol, Xanthan Gum, Disodium EDTA, Rosmarinus Officinalis (Rosemary) Leaf Extract, Anthemis Nobilis Flower Extract, Glyceryl Caprylate, Stearic Acid, Disodium Cetearyl Sulfosuccinate, Aluminum Hydroxide, Hydrated Silica, Cyanocobalamin, Bixa Orellana Seed Oil, Astaxanthin, Bixa Orellana Seed Oil, Ligularia Fishceria Leaf Extract, Ceramide 3, Aloe Barbadensis Leaf Extract, Mentha Piperita (Peppermint) Leaf Extract, Lavandula Angustifolia (Lavender) Flower Extract, Monarda Didyma Leaf Extract, Melissa Officinalis Leaf Extract, Chamomilla Recutita (Matricaria) Leaf Extract, Rosa Centifolia Flower Extract, Palmitoyl Tetrapeptide

PURPOSE

Purpose: Anti wrinkle

WARNINGS

Warnings: For external use only Avoid contact with eyes. Discontinue use if signs of irritation or rashes appear. Replace the cap after use. Keep Out of Reach of Children. Avoid use in areas affected by wounds.

KEEP OUT OF REACH OF CHILDREN

Uses

Uses: Helps prevent wrinkles

Directions

Directions: After washing your face in the morning and at night, apply our toner to tighten pores, and evenly apply an appropriate amount of the serum to the entire face.